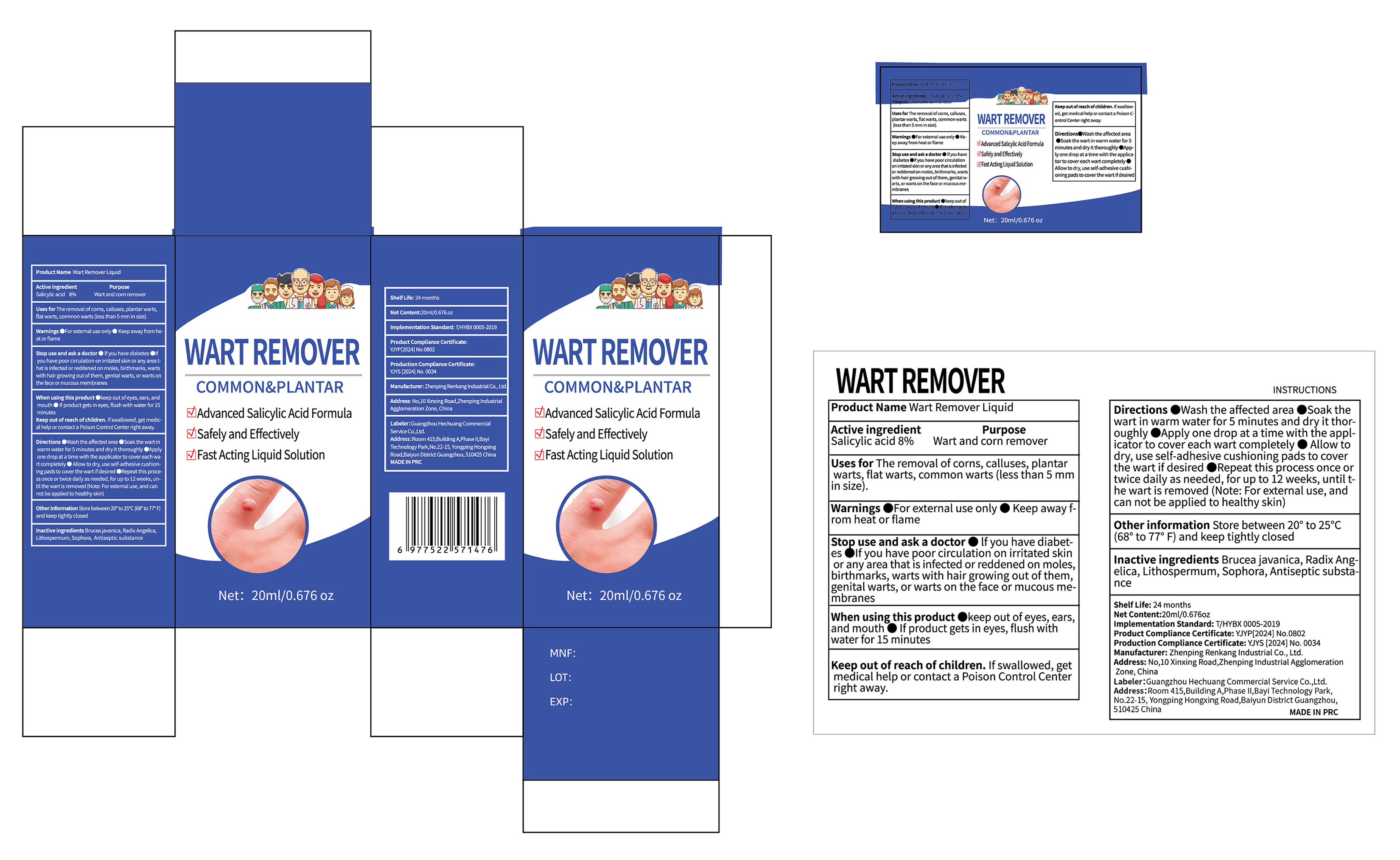 DRUG LABEL: Wart Remover Liquid
NDC: 87298-012 | Form: LIQUID
Manufacturer: Guangzhou Hechuang Commercial Service Co.,Ltd.
Category: otc | Type: HUMAN OTC DRUG LABEL
Date: 20260103

ACTIVE INGREDIENTS: SALICYLIC ACID 8 g/100 g
INACTIVE INGREDIENTS: ANGELICA SINENSIS ROOT; POVIDONE-IODINE; SOPHORA FLAVESCENS ROOT; LITHOSPERMUM ERYTHRORHIZON ROOT; BRUCEA JAVANICA WHOLE

Active ingredient

Salicylic Acid 8%

Purpose

Wart and corn remover

Ingredients

Brucea javanica, Radix Angelica, Lithospermum, Sophora, Antiseptic substance

Uses

Uses for The removal of corns,calluses,plantar warts,flat warts,common warts(less than 5mm in size).

Directions

●Wash the affected area
●Soak the wart ing warm water for 5 minutes and dry it thoroughly
●Apply one drop at a time with the applicator to cover each wart completely
●Allow to dry,use self-adhesive cushioning pads to cover the wart if desired
●Repeat this process once or twice daily as needed,for up to 12 weeks,until the wart is removed(Note:For external use,and can not be applied to healthy skin)

When using this product

●Keep out of eyes,ears,and mouth
●If product gets in eyes,flush with water for 15 minutes

Directions

●Wash the affected area
●Soak the wart ing warm water for 5 minutes and dry it thoroughly
●Apply one drop at a time with the applicator to cover each wart completely
●Allow to dry,use self-adhesive cushioning pads to cover the wart if desired
●Repeat this process once or twice daily as needed,for up to 12 weeks,until the wart is removed(Note:For external use,and can not be applied to healthy skin)

Stop use and ask a doctor

●If you have diabetes
●If you have poor circulation on irritated skin or any area that is infected or reddened on moles,birthmarks,warts with hair growing out of them,genital warts,or warts on the face or mucous membranes

Keep out of reach of children.If swallowed,getmedical help or contact a Poison Control Center right away.

Warnings

For external use only
keep away from heat or flame

Other information

Store between 20° to 25℃(68° to 77°F)and keep tightly closed